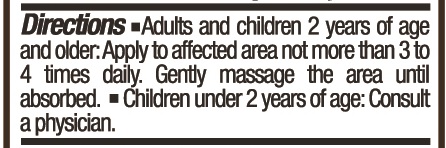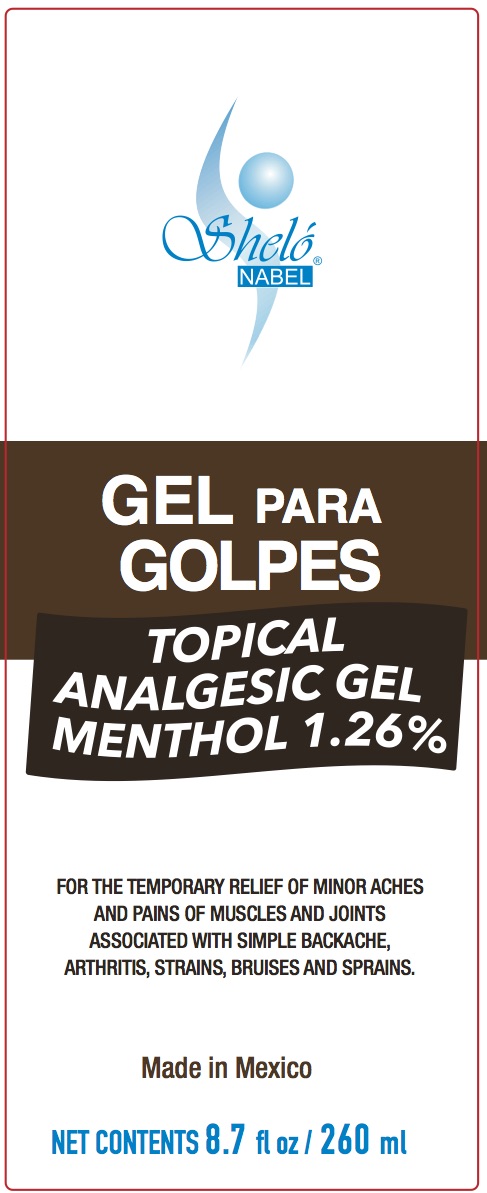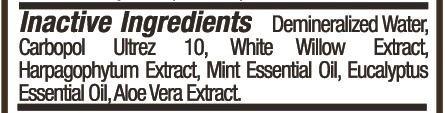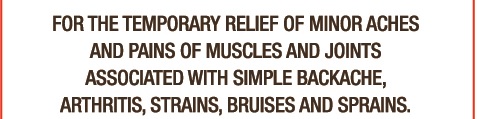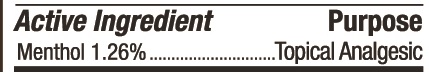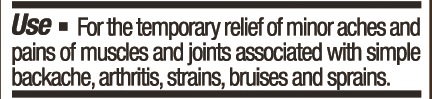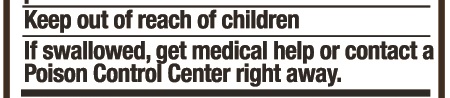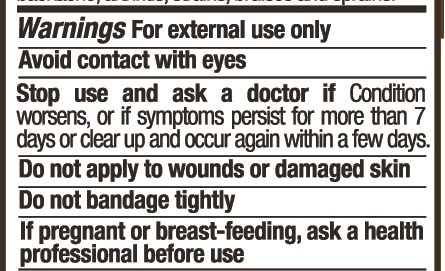 DRUG LABEL: Shelo NABEL Gel para Golpes
NDC: 71424-1347 | Form: GEL
Manufacturer: Corporativo Serysi S de R L de C V
Category: otc | Type: HUMAN OTC DRUG LABEL
Date: 20191014

ACTIVE INGREDIENTS: MENTHOL, UNSPECIFIED FORM 12.6 mg/1 g
INACTIVE INGREDIENTS: MINT

Sheló NABEL Gel Para Golpes